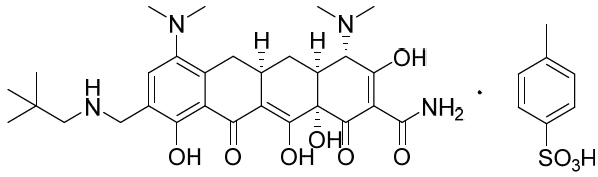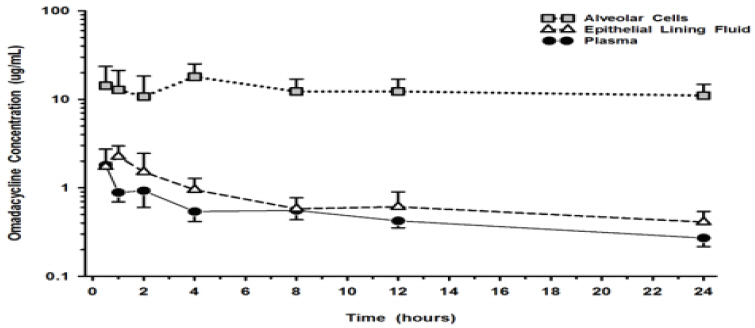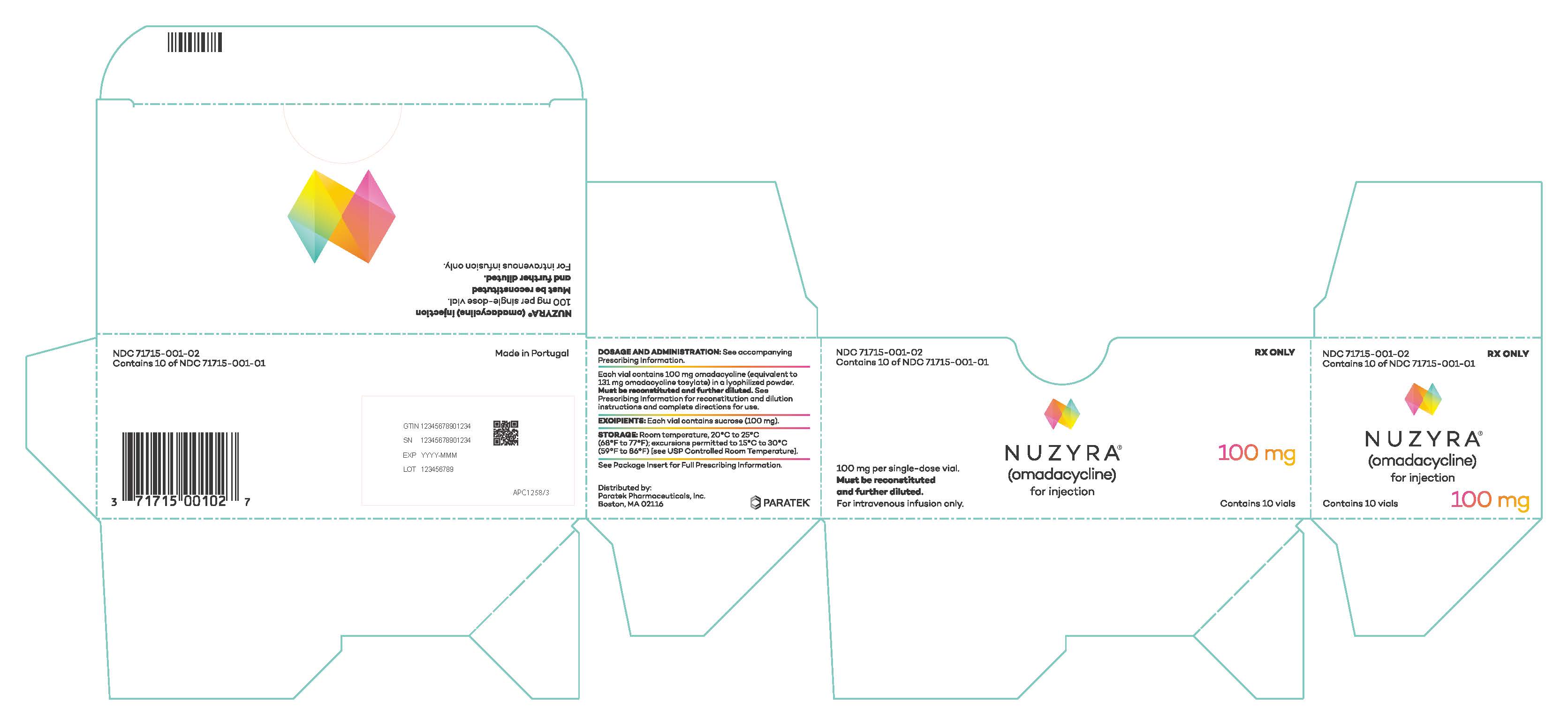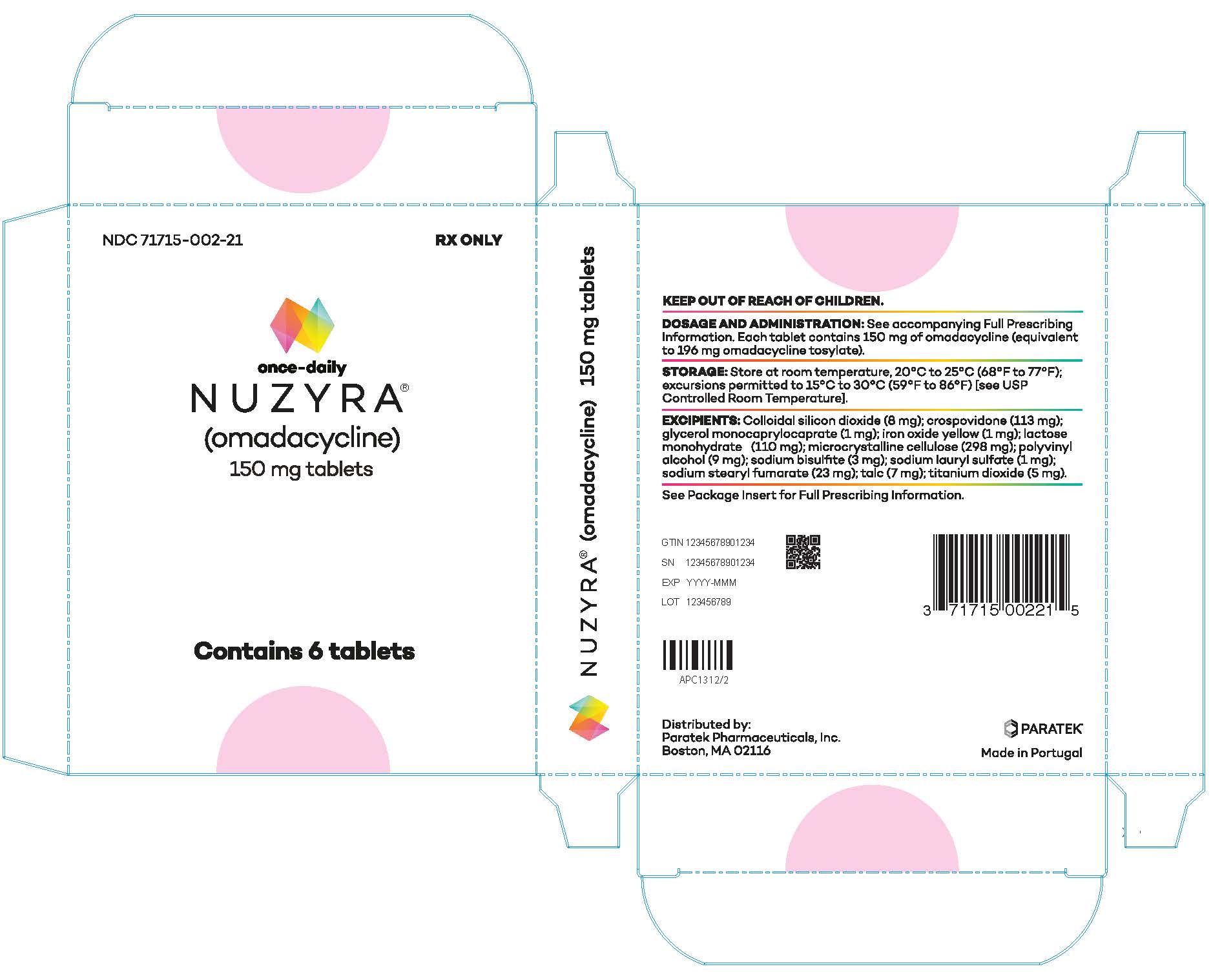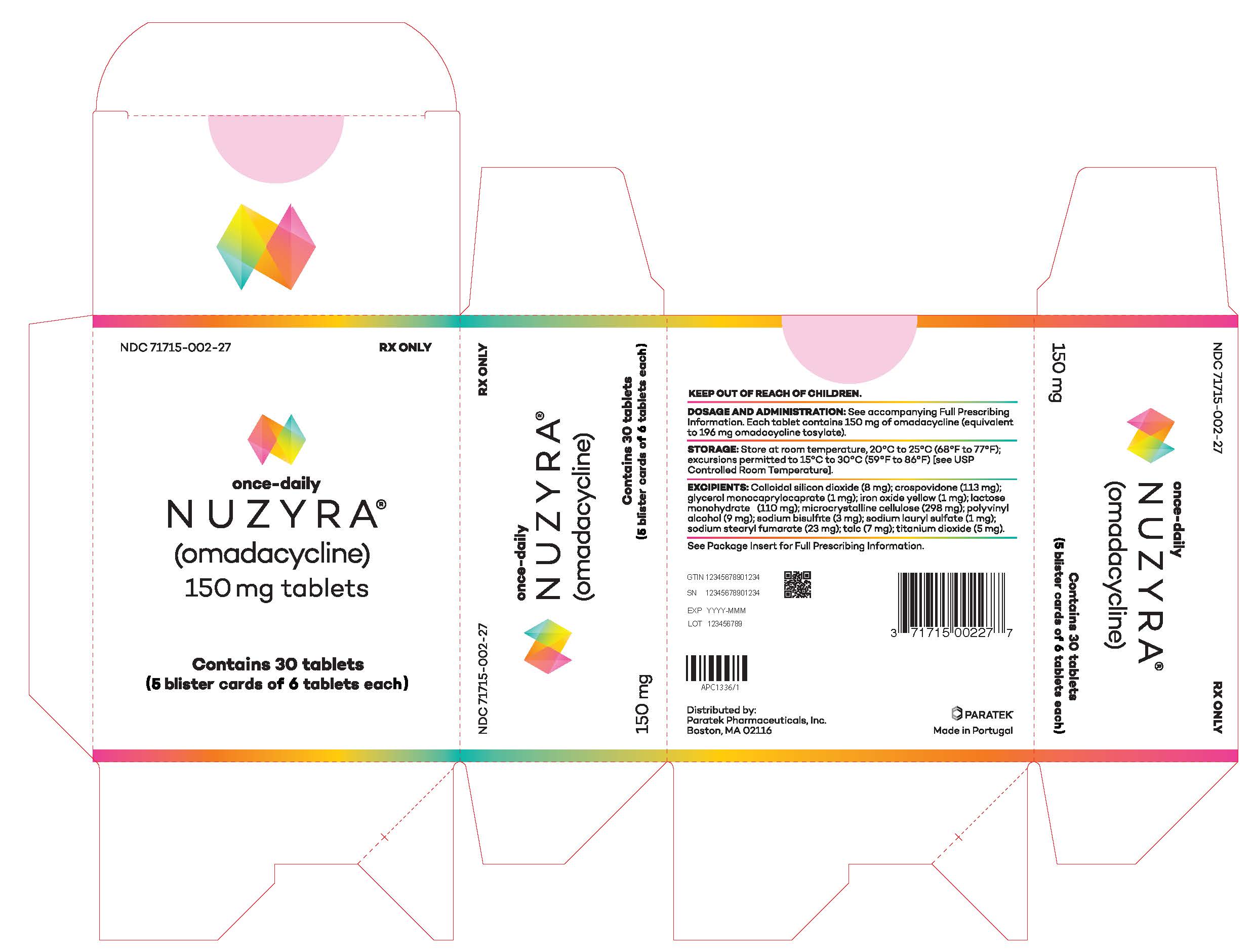 DRUG LABEL: NUZYRA
NDC: 71715-001 | Form: INJECTION, POWDER, LYOPHILIZED, FOR SOLUTION
Manufacturer: Paratek Pharmaceuticals, Inc.
Category: prescription | Type: HUMAN PRESCRIPTION DRUG LABEL
Date: 20250331

ACTIVE INGREDIENTS: OMADACYCLINE 100 mg/5 mL
INACTIVE INGREDIENTS: SUCROSE; HYDROCHLORIC ACID; SODIUM HYDROXIDE; WATER

HIGHLIGHTS OF PRESCRIBING INFORMATION

These highlights do not include all the information needed to use NUZYRA®safely and effectively. See full prescribing information for NUZYRA.
NUZYRA (omadacycline) for injection, for intravenous use
NUZYRA (omadacycline) tablets, for oral use
Initial U.S. Approval: 2018

RECENT MAJOR CHANGES

Warnings and Precautions, Tetracycline Class Effects (5.6) 3/2025

1 INDICATIONS AND USAGE

NUZYRA is a tetracycline class antibacterial indicated for the treatment of adult patients with the following infections caused by susceptible microorganisms (1):

- Community-acquired bacterial pneumonia (CABP) (1.1)
- Acute bacterial skin and skin structure infections (ABSSSI) (1.2)

To reduce the development of drug-resistant bacteria and maintain the effectiveness of NUZYRA and other antibacterial drugs, NUZYRA should be used only to treat or prevent infections that are proven or strongly suspected to be caused by susceptible bacteria. (1.3)

2 DOSAGE AND ADMINISTRATION

- Dosage of NUZYRA in CABP and ABSSSI Adult Patients (2.2, 2.3):

Infection | Loading Doses | Maintenance Dose
CABP | NUZYRA Injection: Day 1: 200 mg by intravenous infusion over 60 minutes OR100 mg by intravenous infusion over 30 minutes twice (2.2) OR NUZYRA Tablets: Day 1: 300 mg orally twice (2.2) | NUZYRA Injection: 100 mg by intravenous infusion over 30 minutes once daily OR NUZYRA Tablets: 300 mg orally once daily (2.2)
ABSSSI | NUZYRA Injection: Day 1: 200 mg by intravenous infusion over 60 minutes OR100 mg by intravenous infusion over 30 minutes twice (2.3) OR NUZYRA Tablets: Day 1 and Day 2: 450 mg orally once daily (2.3) | NUZYRA Injection: 100 mg by intravenous infusion over 30 minutes once daily OR NUZYRA Tablets: 300 mg orally once daily (2.3)

- CABP and ABSSSI: Treatment duration is 7 to 14 days. (2.2, 2.3)
- Fast for at least 4 hours and then take NUZYRA tablets with water. After oral dosing, no food or drink (except water) is to be consumed for 2 hours and no dairy products, antacids, or multivitamins for 4 hours. (2.1)
- See full prescribing information for the preparation of NUZYRA IV and other administration instructions. (2.1, 2.5)

3 DOSAGE FORMS AND STRENGTHS

- For Injection: 100 mg of omadacycline (equivalent to 131 mg omadacycline tosylate) as a lyophilized powder in a single dose vial for reconstitution and further dilution before intravenous infusion (3.1)
- Tablets: 150 mg omadacycline (equivalent to 196 mg omadacycline tosylate) (3.2)

4 CONTRAINDICATIONS

Known hypersensitivity to omadacycline, tetracycline class antibacterial drugs or any of the excipients in NUZYRA (4)

5 WARNINGS AND PRECAUTIONS

- Mortality Imbalance in Patients with CABP: In the CABP trial, mortality rate of 2% was observed in NUZYRA-treated patients compared to 1% in moxifloxacin-treated patients. The cause of the mortality imbalance has not been established. Closely monitor clinical response to therapy in CABP patients, particularly in those at higher risk for mortality. (5.1, 6.1)
- Tooth Discoloration and Enamel Hypoplasia: The use of NUZYRA during tooth development (last half of pregnancy, infancy and childhood to the age of 8 years) may cause permanent discoloration of the teeth (yellow-gray-brown) and enamel hypoplasia. (5.2, 8.1, 8.4)
- Inhibition of Bone Growth:The use of NUZYRA during the second and third trimester of pregnancy, infancy and childhood up to the age of 8 years may cause reversible inhibition of bone growth. (5.3, 8.1, 8.4)
- Clostridioides difficile-associated diarrhea : Evaluate if diarrhea occurs. (5.5)

6 ADVERSE REACTIONS

The most common adverse reactions (incidence ≥2%) are nausea, vomiting, infusion site reactions, alanine aminotransferase increased, aspartate aminotransferase increased, gamma-glutamyl transferase increased, hypertension, headache, diarrhea, insomnia, and constipation. (6.1)

To report SUSPECTED ADVERSE REACTIONS, contact Paratek Pharmaceuticals, Inc. at 1-833-727-2835 or FDA at 1-800-FDA-1088 or www.fda.gov/medwatch.

7 DRUG INTERACTIONS

- Patients who are on anticoagulant therapy may require downward adjustment of their anticoagulant dosage while taking NUZYRA. (7.1)
- Absorption of tetracyclines, including NUZYRA, is impaired by antacids containing aluminum, calcium, or magnesium, bismuth subsalicylate and iron containing preparations. (2.1, 7.2)

8 USE IN SPECIFIC POPULATIONS

Lactation: Breastfeeding is not recommended during treatment with NUZYRA. (8.2)

FULL PRESCRIBING INFORMATION

1 INDICATIONS AND USAGE

1.1 Community-Acquired Bacterial Pneumonia (CABP)

NUZYRA is indicated for the treatment of adult patients with community-acquired bacterial pneumonia (CABP) caused by the following susceptible microorganisms: Streptococcus pneumoniae, Staphylococcus aureus(methicillin-susceptible isolates), Haemophilus influenzae, Haemophilus parainfluenzae, Klebsiella pneumoniae, Legionella pneumophila, Mycoplasma pneumoniae, and Chlamydophila pneumoniae.

1.2 Acute Bacterial Skin and Skin Structure Infections (ABSSSI)

NUZYRA is indicated for the treatment of adult patients with acute bacterial skin and skin structure infections (ABSSSI) caused by the following susceptible microorganisms: Staphylococcus aureus(methicillin-susceptible and -resistant isolates), Staphylococcus lugdunensis, Streptococcus pyogenes, Streptococcus anginosus grp. (includes S. anginosus, S. intermedius, and S. constellatus), Enterococcus faecalis, Enterobacter cloacae,and Klebsiella pneumoniae.

1.3 Usage

To reduce the development of drug-resistant bacteria and maintain the effectiveness of NUZYRA and other antibacterial drugs, NUZYRA should be used only to treat or prevent infections that are proven or strongly suspected to be caused by susceptible bacteria. When culture and susceptibility information are available, they should be considered in selecting or modifying antibacterial therapy. In the absence of such data, local epidemiology and susceptibility patterns may contribute to the empiric selection of therapy.

2 DOSAGE AND ADMINISTRATION

2.1 Important Administration Instructions

NUZYRA for Injection: Do NOT administer NUZYRA for injection with any solution containing multivalent cations, e.g., calcium and magnesium, through the same intravenous line [see Drug Interactions (7.2)] . Co-infusion with other medications has not been studied [see Dosage and Administration (2.5)] .

NUZYRA Tablets: Fast for at least 4 hours and then take with water. After oral dosing, no food or drink (except water) is to be consumed for 2 hours and no dairy products, antacids, or multivitamins for 4 hours [see Drug Interactions (7.2)and Clinical Pharmacology (12.3)].

2.2 Dosage in Adults with Community-Acquired Bacterial Pneumonia (CABP)

For treatment of adults with CABP the recommended dosage regimen (loading and maintenance) of NUZYRA is described in Table 1 below.

Table 1: Dosage of NUZYRA in Adult CABP Patients
Loading Doses | Maintenance Dose | Treatment Duration
NUZYRA Injection: 200 mg by intravenous infusion over 60 minutes on day 1. OR 100 mg by intravenous infusion over 30 minutes, twice on day 1. OR | NUZYRA Injection: 100 mg by intravenous infusion over 30 minutes once daily. OR NUZYRA Tablets: 300 mg orally once daily. | 7 to 14 Days
NUZYRA Tablets: 300 mg orally twice on day 1.

2.3 Dosage in Adults with Acute Bacterial Skin Structure and Skin Infections (ABSSSI)

For treatment of adults with ABSSSI, the recommended dosage regimen (loading and maintenance) of NUZYRA is described in Table 2 below.

Table 2: Dosage of NUZYRA in Adult ABSSSI Patients
Loading Doses | Maintenance Dose | Treatment Duration
NUZYRA Injection: 200 mg by intravenous infusion over 60 minutes on day 1. OR 100 mg by intravenous infusion over 30 minutes, twice on day 1. OR | NUZYRA Injection: 100 mg by intravenous infusion over 30 minutes once daily. OR NUZYRA Tablets: 300 mg orally once daily. | 7 to 14 Days
NUZYRA Tablets: 450 mg orally once a day on day 1 and day 2.

2.4 Dosage Adjustments in Patients with Renal or Hepatic Impairment

No dosage adjustment is warranted in patients with renal or hepatic impairment [see Clinical Pharmacology (12.3)].

2.5 Preparation and Administration of NUZYRA for Injection Intravenous Solution

Reconstitution and Dilution:

- NUZYRA must be reconstituted and then further diluted under aseptic conditions. To prepare the required dose for intravenous infusion, reconstitute and dilute the appropriate number of vials, as determined from Table 3 below.
- Reconstitute each 100 mg vial of NUZYRA with 5 mL of Sterile Water, 0.9% Sodium Chloride Injection, USP, or 5% Dextrose Injection, USP, for Injection.
- Gently swirl the contents and let the vial stand until the cake has completely dissolved and any foam disperses. Do not shake the vial.
- The reconstituted NUZYRA solution should be yellow to dark orange in color; if not, the solution should be discarded. Visually inspect the reconstituted NUZYRA solution for particulate matter and discoloration prior to further dilution and administration. If necessary, invert the vial to dissolve any remaining powder and swirl gently to prevent foaming.
- Immediately (within 1 hour), withdraw 5 mL or 10 mL of the reconstituted solution and further dilute to a 100 mL (nominal volume) of 0.9% Sodium Chloride Injection, USP, or 5% Dextrose Injection, USP, bag for injection. The concentration of the final diluted infusion solution will either be 1 mg/mL or 2 mg/mL in accordance with Table 3 below. Discard any unused portion of the reconstituted solution.
- Parenteral drug products should be inspected visually for particulate matter and discoloration prior to administration, whenever solution and container permit.

Table 3: Preparation of NUZYRA Intravenous Infusion
NUZYRA for Injection Dose | Number of Vials to Reconstitute for Further Dilution | Volume of Reconstituted Solution (5 mL/vial) to Withdraw for Further Dilution | Final Infusion Concentration of NUZYRA
200 mg | 2 Vials | 10 mL | 2 mg/mL
100 mg | 1 Vial | 5 mL | 1 mg/mL

Storage of the Diluted Infusion Solution

The NUZYRA diluted infusion solution may be used within 24 hours at room temperature (less than or equal to 25°C) or within 7 days when refrigerated (2°C to 8°C). Do not freeze. Allow the infusion bag to reach room temperature prior to use.

Administration

After reconstitution and dilution, administer NUZYRA by intravenous infusion, using a total infusion time of 60 minutes for a 200 mg dose, or a total infusion time of 30 minutes for a 100 mg dose [see Dosage and Administration (2.2, 2.3)] .

Administer NUZYRA intravenously through a dedicated line or through a Y-site. If the same intravenous line is used for sequential infusion of several drugs, the line should be flushed with 0.9% Sodium Chloride Injection, USP, or 5% Dextrose Injection, USP, before and after infusion of NUZYRA. The compatibility of NUZYRA with other drugs and infusion solutions other than 5% Dextrose Injection, USP or 0.9% Sodium Chloride Injection, USP has not been established.

3 DOSAGE FORMS AND STRENGTHS

3.1 NUZYRA for Injection

Each single-dose vial contains 100 mg omadacycline (equivalent to 131 mg omadacycline tosylate) which must be reconstituted and further diluted prior to intravenous infusion. The lyophilized powder is a yellow to dark orange cake.

3.2 NUZYRA Tablets

Each tablet contains 150 mg of omadacycline (equivalent to 196 mg omadacycline tosylate) in yellow, diamond-shaped, film-coated tablets debossed with OMC on one side and 150 on the other side.

4 CONTRAINDICATIONS

NUZYRA is contraindicated in patients with known hypersensitivity to omadacycline or tetracycline class antibacterial drugs, or to any of the excipients [see Warnings and Precautions (5.3)and Adverse Reactions (6.1)].

5 WARNINGS AND PRECAUTIONS

5.1 Mortality Imbalance in Patients with Community-Acquired Bacterial Pneumonia

Mortality imbalance was observed in the CABP clinical trial with eight deaths (2%) occurring in patients treated with NUZYRA compared to four deaths (1%) in patients treated with moxifloxacin. The cause of the mortality imbalance has not been established.

All deaths, in both treatment arms, occurred in patients >65 years of age; most patients had multiple comorbidities [see Use in Specific Populations (8.5)] . The causes of death varied and included worsening and/or complications of infection and underlying conditions. Closely monitor clinical response to therapy in CABP patients, particularly in those at higher risk for mortality [see Adverse Reactions (6.1)].

5.2 Tooth Discoloration and Enamel Hypoplasia

The use of NUZYRA during tooth development (last half of pregnancy, infancy, and childhood up to the age of 8 years) may cause permanent discoloration of the teeth (yellow-gray-brown). This adverse reaction is more common during long-term use of the tetracycline class drugs, but it has been observed following repeated short-term courses. Enamel hypoplasia has also been reported with tetracycline class drugs. Advise the patient of the potential risk to the fetus if NUZYRA is used during the second or third trimester of pregnancy [see Use in Specific Populations (8.1, 8.4)].

5.3 Inhibition of Bone Growth

The use of NUZYRA during the second and third trimester of pregnancy, infancy and childhood up to the age of 8 years may cause reversible inhibition of bone growth. All tetracyclines form a stable calcium complex in any bone-forming tissue. A decrease in fibula growth rate has been observed in premature infants given oral tetracycline in doses of 25 mg/kg every 6 hours. This reaction was shown to be reversible when the drug was discontinued. Advise the patient of the potential risk to the fetus if NUZYRA is used during the second or third trimester of pregnancy [see Use in Specific Populations (8.1, 8.4)] .

5.4 Hypersensitivity Reactions

Hypersensitivity reactions have been reported with NUZYRA [see Adverse Reactions (6.1)]. Life-threatening hypersensitivity (anaphylactic) reactions have been reported with other tetracycline class antibacterial drugs. NUZYRA is structurally similar to other tetracycline class antibacterial drugs and is contraindicated in patients with known hypersensitivity to tetracycline class antibacterial drugs [see Contraindications (4)] . Discontinue NUZYRA if an allergic reaction occurs.

5.5 Clostridioides difficile-Associated Diarrhea

Clostridioides difficile-associated diarrhea (CDAD) has been reported with use of nearly all antibacterial agents and may range in severity from mild diarrhea to fatal colitis. Treatment with antibacterial agents alters the normal flora of the colon leading to overgrowth of C. difficile.

C. difficile produces toxins A and B which contribute to the development of CDAD. Hypertoxin producing strains of C. difficile cause increased morbidity and mortality, as these infections can be refractory to antimicrobial therapy and may require colectomy. CDAD must be considered in all patients who present with diarrhea following antibacterial drug use. Careful medical history is necessary since CDAD has been reported to occur over two months after the administration of antibacterial agents.

If CDAD is suspected or confirmed, ongoing antibacterial drug use not directed against C. difficile may need to be discontinued. Appropriate fluid and electrolyte management, protein supplementation, antibacterial drug treatment of C. difficile, and surgical evaluation should be instituted as clinically indicated.

5.6 Tetracycline Class Effects

NUZYRA is structurally similar to tetracycline class of antibacterial drugs and may have similar adverse reactions. Adverse reactions including photosensitivity, fixed drug eruption, pseudotumor cerebri, and anti-anabolic action which has led to increased BUN, azotemia, acidosis, hyperphosphatemia, pancreatitis, and abnormal liver function tests, have been reported for other tetracycline class antibacterial drugs, and may occur with NUZYRA. Discontinue NUZYRA if any of these adverse reactions are suspected.

5.7 Development of Drug-Resistant Bacteria

Prescribing NUZYRA in the absence of a proven or strongly suspected bacterial infection is unlikely to provide benefit to the patient and increases the risk of the development of drug-resistant bacteria [see Indications and Usage (1.3)].

6 ADVERSE REACTIONS

The following clinically significant adverse reactions are described in greater detail in the Warnings and Precautions section of labeling:

- Mortality Imbalance in Patients with Community-Acquired Bacterial Pneumonia [see Warnings and Precautions (5.1)]
- Tooth Development and Enamel Hypoplasia [see Warnings and Precautions (5.2)]
- Inhibition of Bone Growth [see Warnings and Precautions (5.3)]
- Hypersensitivity Reactions [see Warnings and Precautions (5.4)]
- Tetracycline Class Effects [see Warnings and Precautions (5.6)]

6.1 Clinical Trials Experience

Because clinical trials are conducted under widely varying conditions, adverse reaction rates observed in the clinical trials of a drug cannot be directly compared to rates in the clinical trials of another drug and may not reflect the rates observed in practice.

Overview of the Safety Evaluation of NUZYRA

NUZYRA was evaluated in three Phase 3 clinical trials (Trial 1, Trial 2 and Trial 3). These trials included a single Phase 3 trial in CABP patients (Trial 1) and two Phase 3 trials in ABSSSI patients (Trial 2 and Trial 3). Across all Phase 3 trials, a total of 1073 patients were treated with NUZYRA (382 patients in Trial 1 and 691 in Trials 2 and 3 of which 368 patients were treated with only oral NUZYRA).

Clinical Trial Experience in Patients with Community-Acquired Bacterial Pneumonia

Trial 1 was a Phase 3 CABP trial that enrolled 774 adult patients, 386 randomized to NUZYRA (382 received at least one dose of NUZYRA and 4 patients did not receive the study drug) and 388 randomized to moxifloxacin (all 388 received at least one dose of moxifloxacin). The mean age of patients treated with NUZYRA was 61 years (range 19 to 97 years) and 42% were greater than or equal to 65 years of age. Overall, patients treated with NUZYRA were predominantly male (53.7%), white (92.4%), and had a mean body mass index (BMI) of 27.3 kg/m^2. Approximately 47% of NUZYRA treated patients had CrCl <90 ml/min. Patients were administered an IV to oral switch dosage regimen of NUZYRA. The total treatment duration was 7 to 14 days. Mean duration of IV treatment was 5.7 days and mean total duration of treatment was 9.6 days in both treatment arms.

Imbalance in Mortality

In Trial 1, eight deaths (2%) occurred in 382 patients treated with NUZYRA as compared to four deaths (1%) in 388 patients treated with moxifloxacin. All deaths, in both treatment arms, occurred in patients >65 years of age. The causes of death varied and included worsening and/or complications of infection and underlying conditions. The cause of the mortality imbalance has not been established [see Warnings and Precautions (5.1)] .

Serious Adverse Reactions and Adverse Reactions Leading to Discontinuation

In Trial 1, a total of 23/382 (6.0%) patients treated with NUZYRA and 26/388 (6.7%) patients treated with moxifloxacin experienced serious adverse reactions.

Discontinuation of treatment due to any adverse reactions occurred in 21/382 (5.5%) patients treated with NUZYRA and 27/388 (7.0%) patients treated with moxifloxacin.

Most Common Adverse Reactions

Table 4 lists the most common adverse reactions occurring in ≥2% of patients receiving NUZYRA in Trial 1.

Table 4: Adverse Reactions Occurring in ≥2% of Patients Receiving NUZYRA in Trial 1
Adverse Reaction | NUZYRA (N = 382) | Moxifloxacin (N = 388)
Alanine aminotransferase increased | 3.7 | 4.6
Hypertension | 3.4 | 2.8
Gamma-glutamyl transferase increased | 2.6 | 2.1
Insomnia | 2.6 | 2.1
Vomiting | 2.6 | 1.5
Constipation | 2.4 | 1.5
Nausea | 2.4 | 5.4
Aspartate aminotransferase increased | 2.1 | 3.6
Headache | 2.1 | 1.3

Clinical Trials Experience in Patients with Acute Bacterial Skin and Skin Structure Infections

Trial 2 was a Phase 3 ABSSSI trial that enrolled 655 adult patients, 329 randomized to NUZYRA and 326 randomized to linezolid. Trial 3 was a Phase 3 ABSSSI trial that enrolled 735 adult patients, 368 randomized to NUZYRA and 367 randomized to linezolid.

In Trial 2 (IV to oral switch trial), the mean age of patients treated with NUZYRA was 47 years (range 19 to 88). Overall, patients treated with NUZYRA were predominantly male (62.8%), white (91.0%) and had a mean BMI of 28.1 kg/m^2.

In Trial 3 (oral only trial), the mean age of patients was 43 years (range 18 to 86). Patients treated with NUZYRA were predominantly male (65.8%), white (88.9%), and had a mean BMI of 27.9 kg/m^2.

In Trials 2 and 3, approximately 12% of NUZYRA treated patients had CrCl <90 ml/min. Overall, the mean and median calculated lesion area was similar across both trials. Trial 2 required at least 3 days of IV treatment followed by switch to oral regimen based on physician's discretion. Mean duration of IV treatment in Trial 2 was 4 days and mean total duration of treatment was 9 days in both treatment arms. In Trial 3, only oral therapy was administered, and mean total duration of treatment was 8 days in both treatment arms. The median days on treatment in the pooled ABSSSI trials was 9 days for both NUZYRA and linezolid.

Serious Adverse Reactions and Adverse Reactions Leading to Discontinuation

In the pooled ABSSSI trials, serious adverse reactions occurred in 16/691 (2.3%) of patients treated with NUZYRA and 13/689 (1.9%) of patients treated with comparator. Discontinuation of treatment due to adverse events occurred in 12 (1.7%) NUZYRA treated patients, and 10 (1.5%) comparator treated patients. There was 1 death (0.1%) reported in NUZYRA treated patients and 3 deaths (0.4%) reported in linezolid patients in ABSSSI trials.

Most Common Adverse Reactions

Table 5 includes the most common adverse reactions occurring in ≥2% of patients receiving NUZYRA in Trials 2 and 3.

Table 5: Adverse Reactions Occurring in ≥2% of Patients Receiving NUZYRA in Pooled Trials 2 and 3
Adverse Reaction | NUZYRA (N = 691) | Linezolid (N = 689)
Nausea [In Trial 2, which included IV to oral dosing of NUZYRA, 40 (12%) patients experienced nausea and 17 (5%) patients experienced vomiting in NUZYRA treatment group as compared to 32 (10%) patients experienced nausea and 16 (5%) patients experienced vomiting in the comparator group. One patient (0.3%) in the NUZYRA group discontinued treatment due to nausea and vomiting. In Trial 3, which included the oral loading dose of NUZYRA, 111 (30%) patients experienced nausea and 62 (17%) patients experienced vomiting in NUZYRA treatment group as compared to 28 (8%) patients experienced nausea and 11 (3%) patients experienced vomiting in the linezolid group. One patient (0.3%) in the NUZYRA group discontinued treatment due to nausea and vomiting] | 21.9 | 8.7
Vomiting | 11.4 | 3.9
Infusion site reactions [Infusion site extravasation, pain, erythema, swelling, inflammation, irritation, peripheral swelling and skin induration.] | 5.2 | 3.6
Alanine aminotransferase increased | 4.1 | 3.6
Aspartate aminotransferase increased | 3.6 | 3.5
Headache | 3.3 | 3.0
Diarrhea | 3.2 | 2.9

Selected Adverse Reactions Occurring in Less Than 2% of Patients Receiving NUZYRA in Trials 1, 2 and 3

The following selected adverse reactions were reported in NUZYRA-treated patients at a rate of less than 2% in Trials 1, 2 and 3.

Cardiovascular System Disorders:tachycardia, atrial fibrillation

Blood and Lymphatic System Disorders:anemia, thrombocytosis

Ear and Labyrinth Disorders:vertigo

Gastrointestinal Disorders:abdominal pain, dyspepsia

General Disorders and Administration Site Conditions:fatigue

Immune System Disorders:hypersensitivity

Infections and Infestations:oral candidiasis, vulvovaginal mycotic infection

Investigations:creatinine phosphokinase increased, bilirubin increased, lipase increased, alkaline phosphatase increased

Nervous System Disorders:dysgeusia, lethargy

Respiratory, Thoracic, and Mediastinal disorders:oropharyngeal pain

Skin and Subcutaneous Tissue Disorders:pruritus, erythema, hyperhidrosis, urticaria

7 DRUG INTERACTIONS

7.1 Anticoagulant Drugs

Because tetracyclines have been shown to depress plasma prothrombin activity, patients who are on anticoagulant therapy may require downward adjustment of their anticoagulant dosage while also taking NUZYRA.

7.2 Antacids and Iron Preparations

Absorption of oral tetracyclines, including NUZYRA, is impaired by antacids containing aluminum, calcium, or magnesium, bismuth subsalicylate, and iron containing preparations [see Dosage and Administration (2.1)].

8 USE IN SPECIFIC POPULATIONS

8.1 Pregnancy

Risk Summary

NUZYRA, like other tetracycline class antibacterial drugs, may cause discoloration of deciduous teeth and reversible inhibition of bone growth when administered during the second and third trimester of pregnancy [see Warnings and Precautions (5.2, 5.3), Data, Use in Specific Populations (8.4)].

The limited available data of NUZYRA use in pregnant women is insufficient to inform drug associated risk of major birth defects and miscarriages. Animal studies indicate that administration of omadacycline during the period of organogenesis resulted in fetal loss and/or congenital malformations in pregnant rats and rabbits at 7 times and 3 times the mean AUC exposure, respectively, of the clinical intravenous dose of 100 mg and the oral dose of 300 mg. Reductions in fetal weight occurred in rats at all administered doses (see Data). In a fertility study, administration to rats during mating and early pregnancy resulted in embryo loss at 20 mg/kg/day; systemic exposure based on AUC was approximately equal to the clinical exposure level [see Nonclinical Toxicology (13.1)] . Results of studies in rats with omadacycline have shown tooth discoloration.

The estimated background risk of major birth defects and miscarriage for the indicated population is unknown. All pregnancies have a background risk of birth defect, loss, or other adverse outcomes. In the U.S. general population, the estimated background risk of major birth defects and miscarriage in clinically recognized pregnancies is 2 to 4% and 15-20%.

Data

Animal Data

Intravenous infusion of omadacycline to pregnant rats during organogenesis (gestation days 6-17) at doses of 5 to 80 mg/kg/day resulted in maternal lethality at 80 mg/kg/day. Increased embryo-fetal lethality and fetal malformations (whole body edema) occurred at 60 mg/kg/day (7 times the clinical AUC), dose-dependent reductions in fetal body weight occurred at all doses, and delayed skeletal ossification occurred at doses as low as 10 mg/kg/day (Systemic exposure based on AUC at a similar dose in unmated female rats in a separate study was approximately half the clinical exposure). In pregnant rabbits, intravenous infusion of 5, 10 or 20 mg/kg/day during organogenesis (gestation days 7-18) resulted in maternal lethality and body weight loss at 20 mg/kg/day. Embryo-fetal lethality, congenital malformations of the skeleton, and reduced fetal weight also occurred at 20 mg/kg/day (7 times the clinical AUC). Cardiac and lung malformations were present in dose-related incidence at 10 and 20 mg/kg/day. The fetal no-adverse-effect-level in the rabbit embryo-fetal development study was 5 mg/kg/day, at approximately 1.2 times the clinical steady state AUC.

Intravenous infusion of omadacycline to pregnant and lactating rats at doses of 7.5, 15 and 30 mg/kg/day did not adversely affect survival, growth (other than lower pup body weights and/or gains at the high dose that were only statistically significant at sporadic intervals), postnatal development, behavior, or reproductive capability of offspring at maternal doses up to 30 mg/kg/day (approximately equivalent to 3 times the IV clinical dose of 100 mg/day, based on doses normalized for total body surface area), the highest dose tested, although dosing was discontinued early in a number of animals in this group due to injection site intolerance.

Results of animal studies indicate that tetracyclines cross the placenta, are found in fetal tissues, and can have toxic effects on the developing fetus (often related to retardation of skeletal development). Evidence of embryotoxicity also has been noted in animals treated early in pregnancy.

8.2 Lactation

Risk Summary

There is no information on the presence of omadacycline in human milk, the effects on the breastfed infant or the effects on milk production. Tetracyclines are excreted in human milk; however, the extent of absorption of tetracyclines, including omadacycline, by the breastfed infant is not known. Because there are other antibacterial drug options available to treat CABP and ABSSSI in lactating women and because of the potential for serious adverse reactions, including tooth discoloration and inhibition of bone growth, advise patients that breastfeeding is not recommended during treatment with NUZYRA and for 4 days (based on half-life) after the last dose.

8.3 Females and Males of Reproductive Potential

Contraception

Females

NUZYRA may produce embryonic or fetal harm [see Use in Specific Populations (8.1)]. Advise patients to use an acceptable form of contraception while taking NUZYRA.

Infertility

Males

In rat studies, injury to the testis and reduced sperm counts and motility occurred in male rats after treatment with omadacycline [see Nonclinical Toxicology (13.1)].

Females

In rat studies, omadacycline affected fertility parameters in female rats, resulting in reduced ovulation and increased embryonic loss at intended human exposures [see Nonclinical Toxicology (13.1)] .

8.4 Pediatric Use

Safety and effectiveness of NUZYRA in pediatric patients below the age of 18 years have not been established.

Due to the adverse effects of the tetracycline class of drugs, including NUZYRA on tooth development and bone growth, use of NUZYRA in pediatric patients less than 8 years of age is not recommended [see Warnings and Precautions (5.1, 5.2)].

8.5 Geriatric Use

Of the total number of patients who received NUZYRA in the Phase 3 clinical trials (n=1073), 200 patients were ≥65 years of age, including 92 patients who were ≥75 years of age. In Trial 1, numerically lower clinical success rates at early clinical response (ECR) timepoint for NUZYRA-treated and moxifloxacin-treated patients (75.5% and 78.7%, respectively) were observed in CABP patients ≥ 65 years of age as compared to patients <65 years of age (85.2% and 86.3%, respectively). Additionally, all deaths in the CABP trial occurred in patients >65 years of age [see Adverse Reactions (6.1)].

No significant difference in NUZYRA exposure was observed between healthy elderly subjects and younger subjects following a single 100 mg IV dose of NUZYRA [see Clinical Pharmacology (12.3)] .

8.6 Hepatic Impairment

No dose adjustment of NUZYRA is warranted in patients with mild, moderate, or severe hepatic insufficiency (Child-Pugh classes A, B, or C) [see Clinical Pharmacology (12.3)].

8.7 Renal Impairment

No dose adjustment of NUZYRA is warranted in patients with mild, moderate, or severe renal impairment, including patients with end stage renal disease who are receiving hemodialysis [see Clinical Pharmacology (12.3)].

10 OVERDOSAGE

No specific information is available on the treatment of overdosage with NUZYRA. Following a 100 mg single dose intravenous administration of omadacycline, 8.9% of dose is recovered in the dialysate.

11 DESCRIPTION

NUZYRA contains omadacycline tosylate, an aminomethylcycline which is a semisynthetic derivative of the tetracycline class of antibacterial drugs, for intravenous or oral administration. The chemical name of omadacycline tosylate is (4S,4aS,5aR,12aS)-4,7-bis(dimethylamino)-9-(2,2-dimethylpropylaminomethyl)-3,10,12,12a-tetrahydroxy-1,11-dioxo-1,4,4a,5,5a,6,11,12a-octahydrotetracene-2-carboxamide, 4-methylbenzenesulfonate.

The molecular formula is C36H48N4O10S (monotosylate salt) and the molecular weight is 728.9 (monotosylate salt). The following represents the chemical structure of omadacycline tosylate:

NUZYRA (omadacycline) for injection is a yellow to dark orange sterile lyophilized powder. Each vial of NUZYRA for injection contains 100 mg of omadacycline (equivalent to 131 mg omadacycline tosylate). Inactive ingredients: Sucrose (100 mg); may include hydrochloric acid and/or sodium hydroxide for pH adjustment.

NUZYRA (omadacycline) tablets for oral administration are yellow film coated tablets containing 150 mg of omadacycline (equivalent to 196 mg omadacycline tosylate), and the following inactive ingredients: Colloidal silicon dioxide, crospovidone, glycerol monocaprylocaprate, iron oxide yellow, lactose monohydrate, microcrystalline cellulose, polyvinyl alcohol, sodium bisulfite, sodium lauryl sulfate, sodium stearyl fumarate, talc, and titanium dioxide.

12 CLINICAL PHARMACOLOGY

12.1 Mechanism of Action

NUZYRA is an antibacterial drug [see Microbiology (12.4)].

12.2 Pharmacodynamics

Cardiac Electrophysiology

Based on the nonclinical and clinical data, including electrocardiogram evaluation in the phase 3 clinical trials, one of which had moxifloxacin as a control group, no clinically relevant QTc prolongation was observed at the maximum recommended dose of omadacycline.

Cardiac Physiology-Increase in Heart Rate

In phase 1 studies conducted in healthy volunteers, reversible dose-dependent increases in heart rate have been observed following administration of single and multiple doses of omadacycline. The clinical implication of this finding is unknown [see Adverse Reactions (6.1)].

In a standard radiolabeled ligand binding assays, omadacycline was shown to inhibit binding of H-scopolamine to the M2 subtype of the muscarinic acetylcholine receptor. In the heart, muscarinic M2 receptors serve as mediators of the parasympathetic input that normally is received via the vagus nerve and stimulation of the receptor increases membrane potassium conductance through the acetylcholine-dependent channel, which slows depolarization and reduces pacemaker activity in the sinoatrial node.

12.3 Pharmacokinetics

The pharmacokinetic parameters of NUZYRA after single and multiple oral and intravenous doses are summarized in Table 6.

Table 6: Mean (SD) Pharmacokinetic Parameters of NUZYRA in Healthy Adult Subjects
Dose and Route of Administration |  | 100 mg IV | 300 mg Oral | 450 mg Oral
PK Parameters [All PK parameters presented as mean (standard deviation), Number of Subjects, unless otherwise specified]
Cmaxng/mL | Single dose | 1507 (582) (n=63) | 548 (146) (n=103) | 874 (232) (n=24)
Cmaxng/mL | Steady state | 2116 (680) (n=41) | 952 (420) (n=43) | 1077 (269) (n=24)
AUCh*ng/mL | Single dose [Presented as AUC (0-inf)] | 9358 (2072) (n=62) | 9399 (2559) (n=102) | 13504 (3634) (n=24)
AUCh*ng/mL | Steady state [Presented as AUC (0-24)] | 12140 (3223) (n=41) | 11156 (5010) (n=43) | 13367 (3469) (n=24)
Accumulation | Accumulation ratio 1.5
Absorption
Bioavailability | 34.5% following single 300 mg dose of NUZYRA
TmaxMedian (min, max) | Single dose | 0.6 (0.3, 0.7) (n=63) | 2.5 (1, 4.1) (n=103) | 2.5 (1.5, 3) (n=24)
TmaxMedian (min, max) | Steady state | 0.5 (0, 1) (n=41) | 2.5 (0, 8) (n=43) | 2.5 (1.5, 4) (n=24)
Distribution
Plasma Protein Binding | 20%; not concentration dependent
Volume of DistributionL | Single dose | 256 (66) (n=62) | 794 [Presented as apparent clearance or volume of distribution] (188) (n=27) | 914 (821.9) (n=23)
Volume of DistributionL | Steady state | 190 (53) (n=41) | 440 (262) (n=34) | 607 (197.4) (n=24)
Elimination
Elimination Half-Lifeh | Single dose | 16.4 (2.1) (n=62) | 15.0 (2.5) (n=81) | 13.45 (1.7) (n=23)
Elimination Half-Lifeh | Steady state | 16.0 (3.5) (n=41) | 15.5 (1.7) (n=21) | 16.83 (1.4) (n=23)
Systemic ClearanceL/h | Single dose | 11.24 (2.7) (n=62) | 34.6 (10.7) (n=27) | 43.4 (49.8) (n=23)
Systemic ClearanceL/h | Steady state | 8.8 (2.2) (n=41) | 18.3 (8.3) (n=34) | 21.2 (8.9) (n=24)
Renal ClearanceL/h | 3.1 (0.69) (n=8)
Metabolism | Omadacycline is not metabolized
Excretion(% dose) | Urine | 27 (3.5) (n=8) | 14.4 [Following administration of radiolabeled omadacycline] (2.3) (n=6) | ND
Excretion(% dose) | Feces | ND | 81.1 (2.3) (n=6) | ND
Cmax= maximum plasma concentration, AUC = area under concentration-time curve, IV = intravenous, ND = not determined, Tmax= time to Cmax

Absorption

The exposure to omadacycline is similar between a 300 mg oral dose and a 100 mg intravenous dose of NUZYRA in healthy fasted subjects.

Effect of Food

Ingestion of a standard high-fat nondairy meal (855 calories; 59% calories from fat) and standard high-fat meal including dairy (985 calories; 60% calories from fat) 2-hours before administration of a single 300 mg oral dose of NUZYRA decreased the rate (Cmax) and extent of absorption (AUC) by 40% and 42%, and 59% and 63%, respectively compared to administration of NUZYRA under fasting conditions. The rate and extent of absorption of NUZYRA were not substantially decreased when a high-fat nondairy meal (800-1000 calories; 50% calories from fat) was ingested 4 hours pre-dose.

Following ingestion of either a light non-fat (300-350 calories; ≤5% calories from fat), or a standard low-fat (800-1000 calories; 30% calories from fat), or a standard high fat (800-1000 calories; 50% calories from fat) meal 2 hours post-dose, the AUC and Cmaxwere not substantially altered, as compared to fasting conditions.

Distribution

Plasma protein binding of omadacycline is approximately 20% and is not concentration dependent. The mean (% CV) volume of distribution of omadacycline at steady-state following IV administration of NUZYRA in healthy subjects was 190 (27.7) L.

Elimination

Renal clearance of omadacycline following IV administration of NUZYRA ranged from 2.4 to 3.3 L/h in healthy subjects.

Metabolism

In vitrostudies using human liver microsomes and hepatocytes demonstrated that omadacycline is not metabolized.

Excretion

Following a 100 mg IV dose of NUZYRA, 27% of the dose was recovered as unchanged omadacycline in the urine. In healthy male volunteers receiving 300 mg oral [^14C] NUZYRA, 77.5% to 84.0% of the dose was recovered in the feces, approximately 14.4% (range 10.8% to 17.4%) in the urine, with 95.5% of the administered radioactive dose recovered after 7 days.

Lung Penetration

The mean omadacycline concentrations over time for alveolar cells (AC), epithelial lining fluid (ELF), and plasma following IV administration of multiple doses of 100 mg of NUZYRA to healthy volunteers are shown in Figure 1. The steady-state omadacycline AUC0-24h(302.5 hr*mcg/mL) in AC was 25.8-fold higher than the plasma AUC0-24h, and the AUC0-24h(17.2 hr*mcg/mL) in ELF was 1.5-fold higher than the AUC0-24hin plasma.

Figure 1: Mean (± SD) Concentrations of Omadacycline in Alveolar Cells, Epithelial Lining, and Plasma Following Multiple 100 mg IV Doses of NUZYRA to Healthy Subjects During Bronchoscopy Sampling Times

Specific Populations

No clinically significant differences in the pharmacokinetics of omadacycline were observed based on age, gender, race, weight, renal impairment or end-stage renal disease, and hepatic impairment.

Patients with Renal Impairment

A study was conducted to compare NUZYRA pharmacokinetics following 100 mg IV administration in 8 subjects with end-stage renal disease (ESRD) on stable hemodialysis, with and 8-matched healthy control subjects. In the ESRD subjects, NUZYRA was administered on two separate occasions; immediately prior to dialysis and after dialysis, and the AUC, Cmax, and CL of NUZYRA were comparable between the renally impaired subjects and the matching healthy subjects. During dialysis, 7.9% of omadacycline was recovered in the dialysate. Renal impairment did not impact NUZYRA elimination.

Patients with Hepatic Impairment

A study was conducted to compare NUZYRA pharmacokinetics following intravenous and oral dosing to 5 subjects with mild hepatic impairment (Child-Pugh Class A), 6 subjects with moderate hepatic impairment (Child-Pugh Class B), and 6 subjects with severe hepatic impairment (Child-Pugh Class C) as compared to 12 matched healthy control subjects. The AUC and Cmaxof NUZYRA were comparable between the hepatically impaired subjects and the matching healthy subjects, and similar clearance was observed across all cohorts. Hepatic impairment did not impact NUZYRA elimination.

Drug Interaction Studies

Clinical Studies

Administration of oral verapamil (P-gp inhibitor) two hours prior to a single 300 mg oral dose of NUZYRA increased omadacycline AUC by approximately 25% and Cmax by approximately 9%.

In vitro Studies

In vitro studies in human liver microsomes indicate that omadacycline does not inhibit nor induce metabolism mediated by CYP 1A1, 1A2, 2A6, 2B6, 2C8, 2C9, 2C19, 2D6, and 3A4/5, or UGT1A1. Therefore, NUZYRA is not expected to alter the pharmacokinetics of drugs metabolized by the above stated human hepatic enzymes.

Omadacycline is not an inhibitor of P-gp and organic anion transporting polypeptide (OATP) 1B1 and OATP1B3. Omadacycline is a substrate of P-gp (see Clinical Studies above). Omadacycline is not a substrate or inhibitor of the major organic anion transporters (OAT-1 and 3), breast cancer resistance protein (BCRP), or multidrug resistance-associated protein 2 (MRP2). Omadacycline was not an OATP1B1 or OATP1B3 substrate at supra-therapeutic concentrations (5-13 fold higher than clinically relevant concentrations).

12.4 Microbiology

Mechanism of Action

Omadacycline is an aminomethylcycline antibacterial within the tetracycline class of antibacterial drugs. Omadacycline binds to the 30S ribosomal subunit and blocks protein synthesis. In general, omadacycline is considered bacteriostatic; however, omadacycline has demonstrated bactericidal activity against some isolates of S. pneumoniae and H. influenzae.

Resistance

The following in vitro data are available, but their clinical significance is unknown. Omadacycline was active in vitro against Gram-positive bacteria expressing ribosomal protection proteins (TetM) and tetracycline resistance active efflux pumps (TetK and TetL), and in Enterobacteriaceae expressing the TetB efflux pump. Additionally, omadacycline was active against some S. aureus, S. pneumoniae, and H. influenzae strains carrying macrolide resistance genes (ermA, Band/or C), or ciprofloxacin resistance genes (gyrAand parC) and beta-lactamase positive H. influenzae.

Interaction with Other Antimicrobials

In vitro studies have not demonstrated antagonism between omadacycline and other commonly used antibacterials (ampicillin, ceftazidime, ceftriaxone, imipenem, piperacillin/tazobactam, gentamicin, vancomycin, daptomycin, linezolid).

Antimicrobial Activity

Omadacycline has been shown to be active against most isolates of the following bacteria, both in vitro and in clinical infections [see Indications and Usage (1.1, 1.2)] .

Community-Acquired Bacterial Pneumonia (CABP)

- Gram-positive bacteria
  Streptococcus pneumoniae
  Staphylococcus aureus (methicillin-susceptible isolates)

- Gram-negative bacteria
  Haemophilus influenzae
  Haemophilus parainfluenzae
  Klebsiella pneumoniae

- Other microorganisms
  Chlamydophila pneumoniae
  Legionella pneumophila
  Mycoplasma pneumoniae

Acute Bacterial Skin and Skin Structure Infections (ABSSSI)

- Gram-positive bacteria
  Enterococcus faecalis
  Staphylococcus aureus (methicillin-susceptible and -resistant isolates)
  Staphylococcus lugdunensis
  Streptococcus anginosus grp. (includes S. anginosus, S. intermedius, and S. constellatus)
  Streptococcus pyogenes

- Gram-negative bacteria
  Enterobacter cloacae
  Klebsiella pneumoniae

The following in vitro data are available, but their clinical significance is unknown. At least 90% of isolates of the following bacteria exhibit an in-vitro minimum inhibitory concentration (MIC) less than or equal to the susceptible breakpoint for NUZYRA against isolates of similar genus or organism group. However, the efficacy of NUZYRA in treating clinical infections due to these bacteria has not been established in adequate and well controlled clinical trials.

- Gram-positive bacteria
  Enterococcus faecium(vancomycin-susceptible and -resistant isolates)
  Streptococcus agalactiae

- Gram-negative bacteria
  Enterobacter aerogenes
  Escherichia coli
  Citrobacter freundii
  Citrobacter koseri
  Klebsiella oxytoca
  Moraxella catarrhalis

Susceptibility Testing

For specific information regarding susceptibility test interpretive criteria and associated test methods and quality control standards recognized by FDA for this drug, please see: https://www.fda.gov/STIC.

13 NONCLINICAL TOXICOLOGY

13.1 Carcinogenesis, Mutagenesis, Impairment of Fertility

Carcinogenesis

Carcinogenicity studies with omadacycline have not been conducted. However, there has been evidence of oncogenic activity in rats in studies with the related antibacterial drugs, oxytetracycline (adrenal and pituitary tumors), and minocycline (thyroid tumors).

Mutagenesis

Omadacycline was positive for clastogenicity and aneugenicity in an in vitro chromosome aberration assay in Chinese hamster ovary (CHO) cells and for mutagenicity in an in vitro forward mutation assay in mouse lymphoma cells. These effects were seen in the presence of metabolizing enzymes.

Omadacycline was negative in a chromosomal aberration test in Chinese hamster V79 cells and in vivo micronucleus assays administered intraperitoneally to ICR mice or intravenously to HanRcc: WIST rats.

Impairment of Fertility

Omadacycline administration to male rats in a fertility study caused reduced sperm counts and sperm motility at 20-mg/kg/day (approximately 1.3 times clinical systemic exposure, based on AUC in a separate study in rats at a similar dose), but had no effect on male fertility parameters. In general toxicity studies, inhibition of spermatogenesis occurred after administration of 45-mg/kg/day omadacycline (6 to 8 times the clinical AUC exposure) for 37 days or longer, but not at lower doses (15-mg/kg/day, ≤ 2 times clinical AUC exposure) or shorter treatment periods (4 weeks or less). In female rats, fertility was reduced at the 20-mg/kg/day dose (approximately equivalent to human exposures in a separate study in unmated females), characterized by reduced ovulation and increased embryonic loss when treatment occurred from before mating through early pregnancy.

13.2 Animal Toxicology and/or Pharmacology

Hyperpigmentation of the thyroid has been produced by members of the tetracycline class in the following species: in rats by omadacycline, oxytetracycline, doxycycline, tetracycline PO4, and methacycline; in minipigs by doxycycline, minocycline, tetracycline PO4, and methacycline; in dogs by doxycycline and minocycline; in monkeys by omadacycline and minocycline.

Minocycline, tetracycline PO4, methacycline, doxycycline, tetracycline base, oxytetracycline HCl, and tetracycline HCl were goitrogenic in rats fed a low iodine diet. This goitrogenic effect was accompanied by high radioactive iodine uptake. Administration of minocycline also produced a large goiter with high radioiodine uptake in rats fed a relatively high iodine diet.

Treatment of various animal species with this class of drugs has also resulted in the induction of thyroid hyperplasia in the following: in rats and dogs (minocycline); in chickens (chlortetracycline); and in rats and mice (oxytetracycline). Adrenal gland hyperplasia has been observed in goats and rats treated with oxytetracycline.

14 CLINICAL STUDIES

14.1 Community-Acquired Bacterial Pneumonia

A total of 774 adults with CABP were randomized in a multinational, double-blind, double-dummy trial (Trial 1, NCT #02531438) comparing NUZYRA to moxifloxacin. NUZYRA was administered 100 mg intravenously every 12 hours for two doses on Day 1, followed by 100 mg intravenously daily, or 300 mg orally, daily. Moxifloxacin 400 mg was administered intravenously or orally daily. Total treatment duration was 7-14 days. All enrolled patients were expected to require a minimum of at least 3 days of intravenous treatment. Efficacy and safety of an oral loading dose was not evaluated in CABP.

A total of 386 patients were randomized to NUZYRA and 388 patients were randomized to moxifloxacin. Patient demographic and baseline characteristics were balanced between the treatment groups. Patients were predominantly male (55%) and white (92%). Approximately 60% of patients in each group belonged to PORT Risk Class III, 26% were PORT Risk Class IV and 14.5% were PORT Risk Class II. The median age was 62 years, mean BMI was 27.34 kg/m^2, and approximately 47% of NUZYRA treated patients had CrCl <90 ml/min. Among NUZYRA-treated patients, common comorbid conditions included hypertension (49.5%), diabetes mellitus (16.3%), chronic lung disease (21.2%), atrial fibrillation (10.1%), and coronary artery disease (9.1%). The majority of sites were in Eastern Europe, which accounted for 82% of enrollment; 3 patients were enrolled in the US.

Clinical success at the early clinical response (ECR) timepoint, 72 to 120 hours after the first dose, was defined as survival with improvement in at least two of four symptoms (cough, sputum production, chest pain, dyspnea) without deterioration in any of these four symptoms in the intent to treat population (ITT), which consisted of all randomized patients.

Table 7presents the clinical success rates at the ECR timepoint (ITT population).

Table 7: Clinical Success at the ECR Timepoint in Trial 1 (ITT Population)
Endpoint | NUZYRA (%) | Moxifloxacin (%) | Treatment Difference (95% CI [95% confidence interval for the treatment difference])
Clinical Success | 81.1 | 82.7 | -1.6 (-7.1, 3.8)
* Clinical Success at the early clinical response (ECR) timepoint, 72 to 120 hours after the first dose, was defined as survival with improvement in at least two of four symptoms (cough, sputum production, chest pain, dyspnea) from baseline without deterioration in any of these symptoms, with no receipt of antibacterial treatment either as a rescue for CABP or as a treatment for other infections that may be effective for CABP, and no discontinuation of study treatment due to AE.

Clinical response was also assessed by the investigator at the post therapy evaluation visit (PTE), 5 to 10 days after last dose of study drug and defined as survival and improvement in signs and symptoms of CABP, based on the clinician's judgment, to the extent that further antibacterial therapy is not necessary. Table 8 presents the results of clinical response at the PTE visit for both the ITT population and the Clinically Evaluable (CE) population, which consisted of all ITT patients who had a diagnosis of CABP, received a minimum number of expected doses of study drug, did not have any protocol deviations that would affect the assessment of efficacy, and had investigator assessment at the PTE visit. Clinical response rates by most common baseline pathogen in the microbiological ITT (micro-ITT) population, defined as all randomized patients with a baseline pathogen are presented in Table 9.

Table 8: Investigator's Overall Assessment of Clinical Response at PTE [Investigator's overall assessment of clinical response at PTE was defined as survival and improvement in signs and symptoms of CABP, based on the clinician's judgment, to the extent that further antibacterial therapy is not necessary in the ITT and CE populations.] in Trial 1 (ITT and CE Population)
Endpoint | Population | NUZYRA n/N (%) | Moxifloxacin n/N (%) | Treatment Difference (95% CI [95% confidence interval for the treatment difference.])
Clinical Success at PTE | ITT | 338/386 (87.6) | 330/388 (85.1) | 2.5 (-2.4, 7.4)
Clinical Success at PTE | CE | 316/340 (92.9) | 312/345 (90.4) | 2.5 (-1.7, 6.8)

Table 9: Investigator's Overall Assessment of Clinical Response at PTE by Baseline Pathogen in Trial 1 (micro-ITT population)
Pathogen | NUZYRA n/N (%) | Moxifloxacin n/N (%)
Streptococcus pneumoniae | 37/43 (86.0) | 31/34 (91.2)
Methicillin-susceptible Staphylococcus aureus (MSSA) | 8/11 (72.7) | 8/10 (80.0)
Haemophilus influenzae | 26/32 (81.3) | 16/16 (100)
Haemophilus parainfluenzae | 15/18 (83.3) | 13/17 (76.5)
Klebsiella pneumoniae | 10/13 (76.9) | 11/13 (84.6)
Legionella pneumophila | 27/29 (93.1) | 27/28 (96.4)
Mycoplasma pneumoniae | 31/35 (88.6) | 25/29 (86.2)
Chlamydophila pneumoniae | 14/15 (93.3) | 13/14 (92.9)

14.2 Acute Bacterial Skin and Skin Structure Infections

A total of 1390 adults with ABSSSI were randomized in two multicenter, multinational, double-blind, double-dummy trials (Trial 2 NCT #02378480 and Trial 3 NCT #02877927). Both trials compared 7 to 14 days of NUZYRA to linezolid. Patients with cellulitis, major abscess, or wound infection were enrolled in the trials.

In Trial 2, 329 patients were randomized to NUZYRA (100 mg intravenously every 12 hours for 2 doses followed by 100 mg intravenously every 24 hours, with the option to switch to 300 mg orally every 24 hours) and 326 patients were randomized to linezolid (600 mg intravenously every 12 hours, with the option to switch to 600 mg orally every 12 hours). Patients in the trial had the following infections: cellulitis (38%), wound infection (33%), and major abscess (29%). The mean surface area of the infected lesion was 455 cm^2in NUZYRA-treated patients and 498 cm^2in linezolid-treated patients. The mean age of patients was 47 years. Subjects were predominantly male (65%) and white (92%), and mean BMI was 28.1 kg/m^2. Among NUZYRA-treated patients, common comorbid conditions included drug abuse (53.9%), hepatitis C (29.1%), hypertension (20.4%), anxiety (19.5%), and depression (15.5%). Trial 2 was conducted globally including approximately 60% of patients enrolled in the United States.

In Trial 3, 368 patients were randomized to NUZYRA (450 mg oral once a day on Days 1 and 2, followed by 300 mg orally once a day) and 367 were randomized to linezolid (600 mg orally every 12 hours). All patients were enrolled in the United States. Patients in the trial had the following infections: wound infections (58%), cellulitis (24%), and major abscess (18%). The mean surface area of the infected lesion was 424 cm^2in NUZYRA-treated patients and 399 cm^2in linezolid-treated patients. The mean age of patients was 44 years. Subjects were predominantly male (63%) and white (91%) and mean BMI was 27.9 kg/m^2. The most common comorbid conditions included drug abuse (72.8%), tobacco use (12.0%), and chronic hepatitis C infection (31.5%).

In Trials 2 and 3, approximately 12% of NUZYRA-treated patients had CrCl <90 ml/min.

In both trials, efficacy was determined by the successful early clinical response at 48 to 72 hours after the first dose in the mITT population and was defined as a 20% or greater decrease in lesion size. Table 10 summarizes the clinical response rates in the two trials. The mITT population was defined as all randomized subjects without a sole Gram-negative causative pathogen at screening.

Table 10: Clinical Success [Clinical success at early clinical response (ECR) at 48 to 72 hours after the first dose, was defined as a 20% or greater decrease in lesion size without any reasons for failure (less than 20% reduction in lesion size, administration of rescue antibacterial therapy, use of another antibacterial or surgical procedure to treat for lack of efficacy, or death).] at the ECR Timepoint in the mITT Population in Trial 2 and Trial 3
Study | NUZYRA (%) | Linezolid (%) | Treatment Difference (Two-Sided 95% CI) [95% confidence interval for the treatment difference.]
Trial 2 | 84.8 | 85.5 | -0.7 (-6.3, 4.9)
Trial 3 | 87.3 | 82.2 | +5.1 (-0.2, 10.5)

Clinical response at the post therapy evaluation (PTE, 7 to 14 days after last dose) visit in the mITT and clinically evaluable (CE) populations was defined as survival after completion of study treatment without receiving any alternative antibacterial therapy other than NUZYRA, without unplanned major surgical intervention, and sufficient resolution of infection such that further antibacterial therapy is not needed (see Table 11). Clinical response rates at PTE by most common pathogen in the microbiological-mITT population, defined as all patients in the mITT population, who had at least 1 Gram- positive causative pathogen identified at baseline are provided in Table 12. The CE population consisted of all mITT patients who had a diagnosis of ABSSSI, received a minimum number of expected doses of study drug, did not have any protocol deviations that would affect the assessment of efficacy, and had investigator assessment at the PTE Visit.

Table 11: Investigator's Overall Assessment of Clinical Response at PTE in mITT and CE Population in Trial 2 and Trial 3
Study | Population | NUZYRA n/N (%) | Linezolid n/N (%) | Treatment Difference (Two-Sided 95% CI) [95% confidence interval for the treatment difference.]
Trial 2 | mITT | 272/316 (86.1) | 260/311 (83.6) | +2.5 (-3.2, 8.2)
Trial 2 | CE | 259/269 (96.3) | 243/260 (93.5) | +2.8 (-1.0, 6.9)
Trial 3 | mITT | 296/353 (83.9) | 284/353 (80.5) | +3.4 (-2.3, 9.1)
Trial 3 | CE | 272/278 (97.8) | 272/285 (95.4) | +2.4 (-0.6, 5.8)

Table 12: Investigator's Overall Assessment of Clinical Response at PTE by Baseline Pathogen in Trials 2 and 3 (micro-mITT population)
Pathogen | NUZYRA n/N (%) | Linezolid n/N (%)
Staphylococcus aureus | 305/369 (82.7) | 306/378 (81.0)
Methicillin-susceptible Staphylococcus aureus(MSSA) | 164/201 (81.6) | 181/226 (80.1)
Methicillin-resistant Staphylococcus aureus(MRSA) | 146/173 (84.4) | 128/157 (81.5)
Staphylococcus lugdunensis | 10/11 (90.9) | 2/3 (66.7)
Streptococcus anginosusgroup | 84/104 (80.8) | 59/82 (72.0)
Streptococcus pyogenes | 28/40 (70.0) | 25/34 (73.5)
Enterococcus faecalis | 17/18 (94.4) | 21/25 (84.0)
Enterobacter cloacae | 11/14 (78.6) | 9/11 (81.8)
Klebsiella pneumoniae | 8/11 (72.7) | 6/11 (54.5)

16 HOW SUPPLIED/STORAGE AND HANDLING

16.1 How Supplied

NUZYRA for Injection

NUZYRA for Injection is supplied as a sterile lyophilized powder in a single-dose colorless glass vial, with each vial containing 100 mg of NUZYRA (equivalent to 131 mg omadacycline tosylate).

They are supplied as follows: 100 mg single-dose vial (NDC 71715-001-02), packaged in cartons of 10.

NUZYRA Tablets

NUZYRA Tablets contains 150 mg of omadacycline (equivalent to 196 mg omadacycline tosylate) in yellow, diamond-shaped, film-coated tablets debossed with OMC on one side and 150 on the other side.

They are supplied as follows:

Blister package of 6 (NDC 71715-002-21)

Blister package of 30 (5 blister cards of 6 tablets each) (NDC 71715-002-27)

16.2 Storage and Handling

NUZYRA for Injection and NUZYRA Tablets should be stored at 20°C to 25°C (68°F to 77°F); excursions permitted to 15°C to 30°C (59°F to 86°F) [see USP Controlled Room Temperature] [see Dosage and Administration (2.5)]. Do not freeze.

17 PATIENT COUNSELING INFORMATION

Nausea and Vomiting

Advise patients that nausea and vomiting can be an adverse reaction to NUZYRA. Advise patients that a greater proportion of patients who received the oral loading dose of NUZYRA for treatment of ABSSSI experienced nausea and vomiting.

Allergic Reactions

Advise patients that allergic reactions, including serious allergic reactions, could occur and that serious allergic reactions require immediate treatment. Ask the patient about any previous hypersensitivity reactions to NUZYRA, or other tetracycline class antibacterials [see Warnings and Precautions (5.4)] .

Administration with Food

Instruct patients to fast 4 hours before and 2 hours after taking NUZYRA tablets and not to consume dairy products, antacids, or multivitamins for 4 hours after taking NUZYRA tablets [see Dosage and Administration (2.1)and Clinical Pharmacology (12.3)] .

Tooth Discoloration and Inhibition of Bone Growth

Advise patients that NUZYRA, like other tetracycline class drugs, may cause permanent tooth discoloration of deciduous teeth and reversible inhibition of bone growth when administered during the second and third trimesters of pregnancy. Tell your healthcare provider right away if you become pregnant during treatment [see Warnings and Precautions (5.1, 5.2)and Use in Specific Populations (8.1, 8.4)].

Lactation

Advise women not to breastfeed during treatment with NUZYRA and for 4 days after the last dose [see Use in Specific Populations (8.2)].

Diarrhea

Advise patients that diarrhea is a common problem caused by antibacterial drugs, including NUZYRA, which usually ends when the antibacterial drugs is discontinued. Sometimes after starting treatment with antibacterial drugs, patients can develop watery or bloody stools (with or without stomach cramps and fever). If this occurs, patients should contact their physician as soon as possible.

Tetracycline Class Adverse Reactions

Inform patients that NUZYRA is similar to tetracycline class antibacterial drugs and may have similar adverse reactions [see Warnings and Precautions (5.6)] .

Antibacterial Resistance

Advise patients that antibacterial drugs including NUZYRA should only be used to treat bacterial infections. They do not treat viral infections (e.g., the common cold). When NUZYRA is prescribed to treat a bacterial infection, patients should be told that although it is common to feel better early in the course of therapy, the medication should be taken exactly as directed. Skipping doses or not completing the full course of therapy may (1) decrease the effectiveness of the immediate treatment and (2) increase the likelihood that bacteria will develop resistance and will not be treatable by NUZYRA or other antibacterial drugs in the future.

Distributed by:

Paratek Pharmaceuticals, Inc.
Boston, MA, USA

PARATEK®and the hexagon logo are registered trademarks of Paratek Pharmaceuticals, Inc.
NUZYRA®and its design logo are registered trademarks of Paratek Pharmaceuticals, Inc.
For patent information: www.paratekpharma.com/products/patent.
© 2025 Paratek Pharmaceuticals, Inc. All rights reserved.

PRINCIPAL DISPLAY PANEL - 6 Tablet Blister Pack Carton

NDC 71715-002-21
RX ONLY

once-daily
NUZYRA®
(omadacycline)
150 mg tablets

Contains 6 tablets

PRINCIPAL DISPLAY PANEL - 10 Vial Carton

NDC 71715-001-02
Contains 10 of NDC 71715-001-01

RX ONLY

NUZYRA®
(omadacycline)
for injection

100 mg per single-dose vial.
Must be reconstituted
and further diluted.
For intravenous infusion only.

100 mg

Contains 10 vials

PRINCIPAL DISPLAY PANEL - 30 Tablet Blister Pack Carton

NDC 71715-002-27
RX ONLY

once-daily
NUZYRA®
(omadacycline)
150 mg tablets

Contains 30 tablets
(5 blister cards of 6 tablets each)